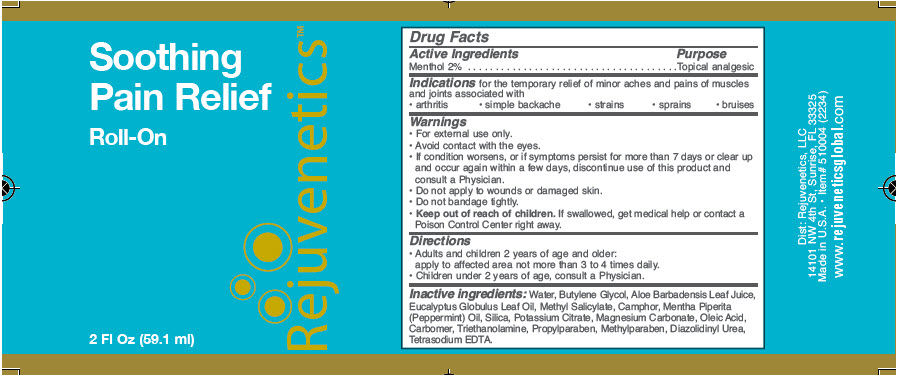 DRUG LABEL: Soothing Pain Relief 
NDC: 64483-008 | Form: GEL
Manufacturer: Clientele, Inc.
Category: otc | Type: HUMAN OTC DRUG LABEL
Date: 20191209

ACTIVE INGREDIENTS: MENTHOL, UNSPECIFIED FORM 2 mg/100 mL
INACTIVE INGREDIENTS: Camphor (synthetic) 0.52 mg/100 mL; Water; Eucalyptus oil

Soothing Pain Relief
Roll On

Drug Facts

Active Ingredients

Menthol 2%

Purpose

Topical analgesic

Indications

for the temporary relief of minor aches and pains of muscles and joints associated with

- arthritis
- simple backache
- strains
- sprains
- bruises

Warnings

- For external use only.

DO NOT USE

- Avoid contact with the eyes.

STOP USE

- If condition worsens, or if symptoms persist for more than 7 days or clear up and occur again within a few days, discontinue use of this product and consult a Physician.

WHEN USING

- Do not apply to wounds or damaged skin.
- Do not bandage tightly.

- Keep out of reach of children. If swallowed, get medical help or contact a Poison Control Center right away.

Directions

- Adults and children 2 years of age and older:
  apply to affected area not more than 3 to 4 times daily.
- Children under 2 years of age, consult a Physician.

Inactive ingredients

Water, Butylene Glycol, Aloe Barbadensis Leaf Juice, Eucalyptus Globulus Leaf Oil, Methyl Salicylate, Camphor, Mentha Piperita (Peppermint) Oil, Silica, Potassium Citrate, Magnesium Carbonate, Oleic Acid, Carbomer, Triethanolamine, Propylparaben, Methylparaben, Diazolidinyl Urea, Tetrasodium EDTA.

PRINCIPAL DISPLAY PANEL - 59.1 ml Bottle Label

Soothing
Pain Relief

Roll-On

2 Fl Oz (59.1 ml)

Rejuvenetics™